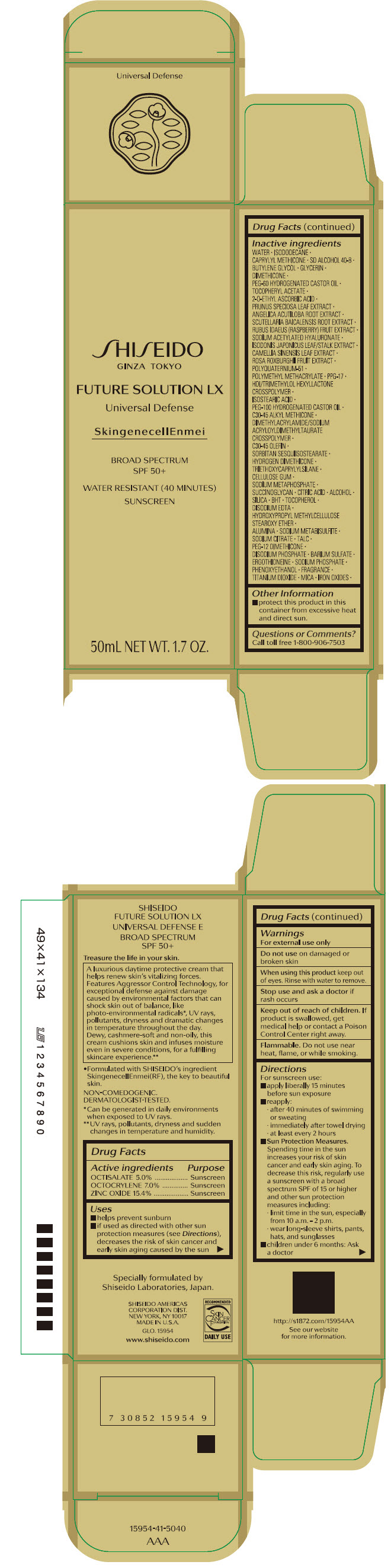 DRUG LABEL: SHISEIDO FUTURE solution LX UNIVERSAL DEFENSE E
NDC: 58411-482 | Form: CREAM
Manufacturer: SHISEIDO AMERICAS CORPORATION
Category: otc | Type: HUMAN OTC DRUG LABEL
Date: 20260105

ACTIVE INGREDIENTS: OCTISALATE 2.523 g/50 mL; OCTOCRYLENE 3.532 g/50 mL; ZINC OXIDE 7.723 g/50 mL
INACTIVE INGREDIENTS: WATER; ISODODECANE; CAPRYLYL TRISILOXANE; BUTYLENE GLYCOL; GLYCERIN; DIMETHICONE; PEG-60 HYDROGENATED CASTOR OIL; .ALPHA.-TOCOPHEROL ACETATE, DL-; 2-O-ETHYL ASCORBIC ACID; PRUNUS SPECIOSA LEAF; ANGELICA ACUTILOBA ROOT; SCUTELLARIA BAICALENSIS ROOT; RASPBERRY; SODIUM ACETYLATED HYALURONATE; GREEN TEA LEAF; ROSA ROXBURGHII FRUIT; POLYQUATERNIUM-51 (2-METHACRYLOYLOXYETHYL PHOSPHORYLCHOLINE/N-BUTYL METHACRYLATE; 3:7); POLY(METHYL METHACRYLATE; 450000 MW); PPG-17; HEXAMETHYLENE DIISOCYANATE/TRIMETHYLOL HEXYLLACTONE CROSSPOLYMER; ISOSTEARIC ACID; C30-45 ALKYL METHICONE; C30-45 OLEFIN; SORBITAN SESQUIISOSTEARATE; HYDROGEN DIMETHICONE (13 CST); TRIETHOXYCAPRYLYLSILANE; CARBOXYMETHYLCELLULOSE SODIUM, UNSPECIFIED; SODIUM POLYMETAPHOSPHATE; CITRIC ACID MONOHYDRATE; ALCOHOL; SILICON DIOXIDE; BUTYLATED HYDROXYTOLUENE; .ALPHA.-TOCOPHEROL; EDETATE DISODIUM; ALUMINUM OXIDE; SODIUM METABISULFITE; SODIUM CITRATE, UNSPECIFIED FORM; TALC; PEG-12 DIMETHICONE (300 CST); SODIUM PHOSPHATE, DIBASIC, ANHYDROUS; BARIUM SULFATE; ERGOTHIONEINE; SODIUM PHOSPHATE; PHENOXYETHANOL; TITANIUM DIOXIDE; MICA; FERRIC OXIDE RED; FERRIC OXIDE YELLOW; FERROSOFERRIC OXIDE

SHISEIDO FUTURE SOLUTION LX UNIVERSAL DEFENSE E

Drug Facts

ACTIVE INGREDIENT

Active ingredients | Purpose
Octisalate 5.0% | Sunscreen
Octocrylene7.0% | Sunscreen
Zinc Oxide 15.4% | Sunscreen

Uses

- helps prevent sunburn
- if used as directed with other sun protection measures (see Directions), decreases the risk of skin cancer and early skin aging caused by the sun

Warnings

For external use only

Do not use on damaged or broken skin

WHEN USING

When using this productkeep out of eyes. Rinse with water to remove.

Stop use and ask a doctorif rash occurs.

Keep out of reach of children.If product is swallowed, get medical help or contact a Poison Control Center right away.

Flammable.Do not use near heat, flame or while smoking.

Directions

For sunscreen use:

- apply liberally 15 minutes before sun exposure
- reapply:
  - after 80 minutes of swimming or sweating
  - immediately after towel drying
  - at least every two hours
- Sun Protection Measures. Spending time in the sun increases your risk of skin cancer and early skin aging. To decrease this risk, regularly use a sunscreen with a broad spectrum SPF of 15 or higher and other sun protection measures including:
  - limit time in the sun, especially from 10 a.m. – 2 p.m.
  - wear long-sleeve shirts, pants, hats, and sunglasses
  - children under 6 months: Ask a doctor

Inactive Ingredients

WATER ▪ ISODODECANE ▪ CAPRYLYL METHICONE ▪ SD ALCOHOL 40-B ▪ BUTYLENE GLYCOL ▪ GLYCERIN ▪ DIMETHICONE ▪ PEG-60 HYDROGENATED CASTOR OIL ▪ TOCOPHERYL ACETATE ▪ 2-O-ETHYL ASCORBIC ACID ▪ PRUNUS SPECIOSA LEAF EXTRACT ▪ ANGELICA ACUTILOBA ROOT EXTRACT ▪ SCUTELLARIA BAICALENSIS ROOT EXTRACT ▪ RUBUS IDAEUS (RASPBERRY) FRUIT EXTRACT ▪ SODIUM ACETYLATED HYALURONATE ▪ ISODONIS JAPONICUS LEAF/STALK EXTRACT ▪ CAMELLIA SINENSIS LEAF EXTRACT ▪ ROSA ROXBURGHII FRUIT EXTRACT ▪ POLYQUATERNIUM-51 ▪ POLYMETHYL METHACRYLATE ▪ PPG-17 ▪ HDI/TRIMETHYLOL HEXYLLACTONE CROSSPOLYMER ▪ ISOSTEARIC ACID ▪ PEG-100 HYDROGENATED CASTOR OIL ▪ C30-45 ALKYL METHICONE ▪ DIMETHYLACRYLAMIDE/SODIUM ACRYLOYLDIMETHYLTAURATE CROSSPOLYMER ▪ C30-45 OLEFIN ▪ SORBITAN SESQUIISOSTEARATE ▪ HYDROGEN DIMETHICONE ▪ TRIETHOXYCAPRYLYLSILANE ▪ CELLULOSE GUM ▪ SODIUM METAPHOSPHATE ▪ SUCCINOGLYCAN ▪ CITRIC ACID ▪ ALCOHOL ▪ SILICA ▪ BHT ▪ TOCOPHEROL ▪ DISODIUM EDTA ▪ HYDROXYPROPYL METHYLCELLULOSE STEAROXY ETHER ▪ ALUMINA ▪ SODIUM METABISULFITE ▪ SODIUM CITRATE ▪ TALC ▪ PEG-12 DIMETHICONE ▪ DISODIUM PHOSPHATE ▪ BARIUM SULFATE ▪ ERGOTHIONEINE ▪ SODIUM PHOSPHATE ▪ PHENOXYETHANOL ▪ FRAGRANCE ▪ TITANIUM DIOXIDE ▪ MICA ▪ IRON OXIDES ▪

Other information

Protect this product in this container from excessive heat and direct sun.

Questions or comments?

Call toll free 1-800-906-7503

PRINCIPAL DISPLAY PANEL - 50 mL Tube Carton

SHISEIDO
GINZA TOKYO

FUTURE SOLUTION LX
Universal Defense

SkingenecellEnmei

BROAD SPECTRUM
SPF 50+

WATER RESISTANT (40 MINUTES)
SUNSCREEN

50mL NET WT. 1.7 OZ.